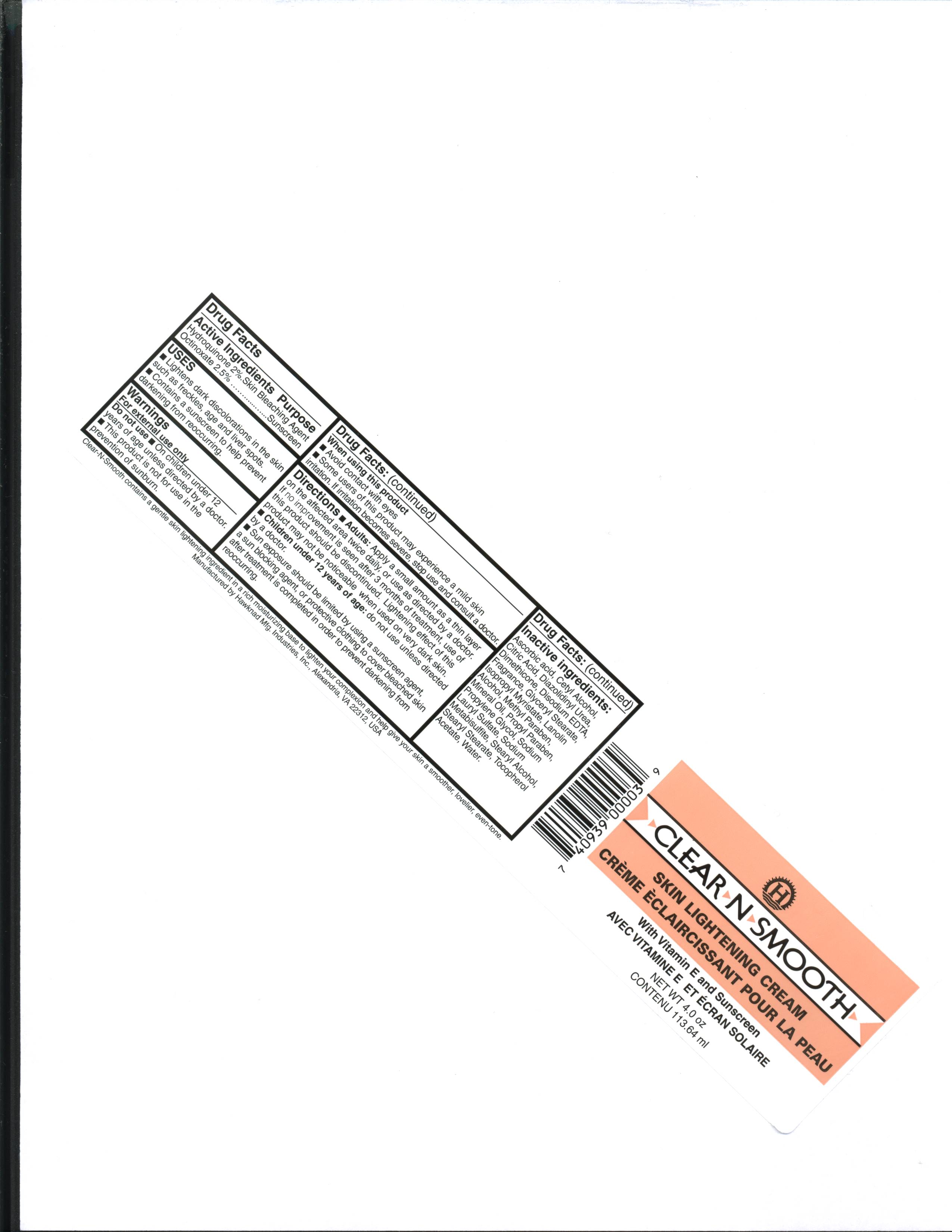 DRUG LABEL: Clear-N-Smooth
NDC: 76445-0043 | Form: CREAM
Manufacturer: Hawknad Manufacturing Industries, Inc.
Category: otc | Type: HUMAN OTC DRUG LABEL
Date: 20191218

ACTIVE INGREDIENTS: HYDROQUINONE 2 g/100 g
INACTIVE INGREDIENTS: GLYCERYL MONOSTEARATE 8.1 g/100 g; SODIUM LAURYL SULFATE 0.3 g/100 g; STEARYL STEARATE 1.5 g/100 g; STEARYL ALCOHOL 3.5 g/100 g; CETYL ALCOHOL 3.5 g/100 g; ISOPROPYL MYRISTATE 4 g/100 g; DIMETHICONE 350 1 g/100 g; .ALPHA.-TOCOPHEROL ACETATE 0.25 g/100 g; OCTINOXATE 3 g/100 g; LIGHT MINERAL OIL 4 g/100 g; ETHYLHEXYL PALMITATE 2 g/100 g; PEG-100 STEARATE 2 dL/100 g; ASCORBIC ACID 0.1 g/100 g; ANHYDROUS CITRIC ACID 0.1 g/100 g; SODIUM METABISULFITE 0.3 g/100 g; METHYLPARABEN 0.1 g/100 g; PROPYLPARABEN 0.1 g/100 g; DIAZOLIDINYL UREA 0.2 g/100 g; WATER 57.6 g/100 g; PROPYLENE GLYCOL 5.6 g/100 g; EDETATE DISODIUM 0.1 g/100 g

Listing for Clear-N-Smooth Skin Lightening Cream

Indications for Use

- Lightens dark colorations in the skin such as freckles, age, and liver spots
- Contains a sunscreen to help prevent darkening from re-occurring.

Purpose

Skin Lightening Cream

Dosage

Moisten a cotton ball and apply a thin layer over the entire affected area.

Keep Out of Reach of Children

Children under 12 years of age: do not use unless directed by a doctor.

Warnings

Do not use on children under 12 years of age unless directed by a doctor.

This product is not for use for the prevention of sunburn.

When using this product avoid contact with eyes.

Some users of this product may experience a mild skin irritation. If irritation becomes severe, stop use and consult a doctor.

Instructions for Use

Apply a small amount as a thin layer on the affected area twice daily, or use as directed by a doctor. If no improvement is seen after 3 months of treatment, use of this product should be discontinued. Lightening effect of this product may not be noticeable when used on very dark skin. Sun exposure should be limited by using a sunscreen agent, a protective clothing to cover bleached skin after treatment is completed in order to prevent darkening from re-occurring.

Inactive Ingredients

ascorbic acid, cetyl alcohol, citric acid, diazolidinyl urea, dimethicone, disodium EDTA, Fragrance, glyceryl stearate, isopropyl myristate, lanolin alcohol, methyl paraben, propyl paraben, mineral oil, propylene glycol, sodium lauryl sulfate, sodium metabisulfite, stearyl alcohol, stearyl stearate, tocopherol acetate, water.

Active Ingredient

Hydroquinone - 2%